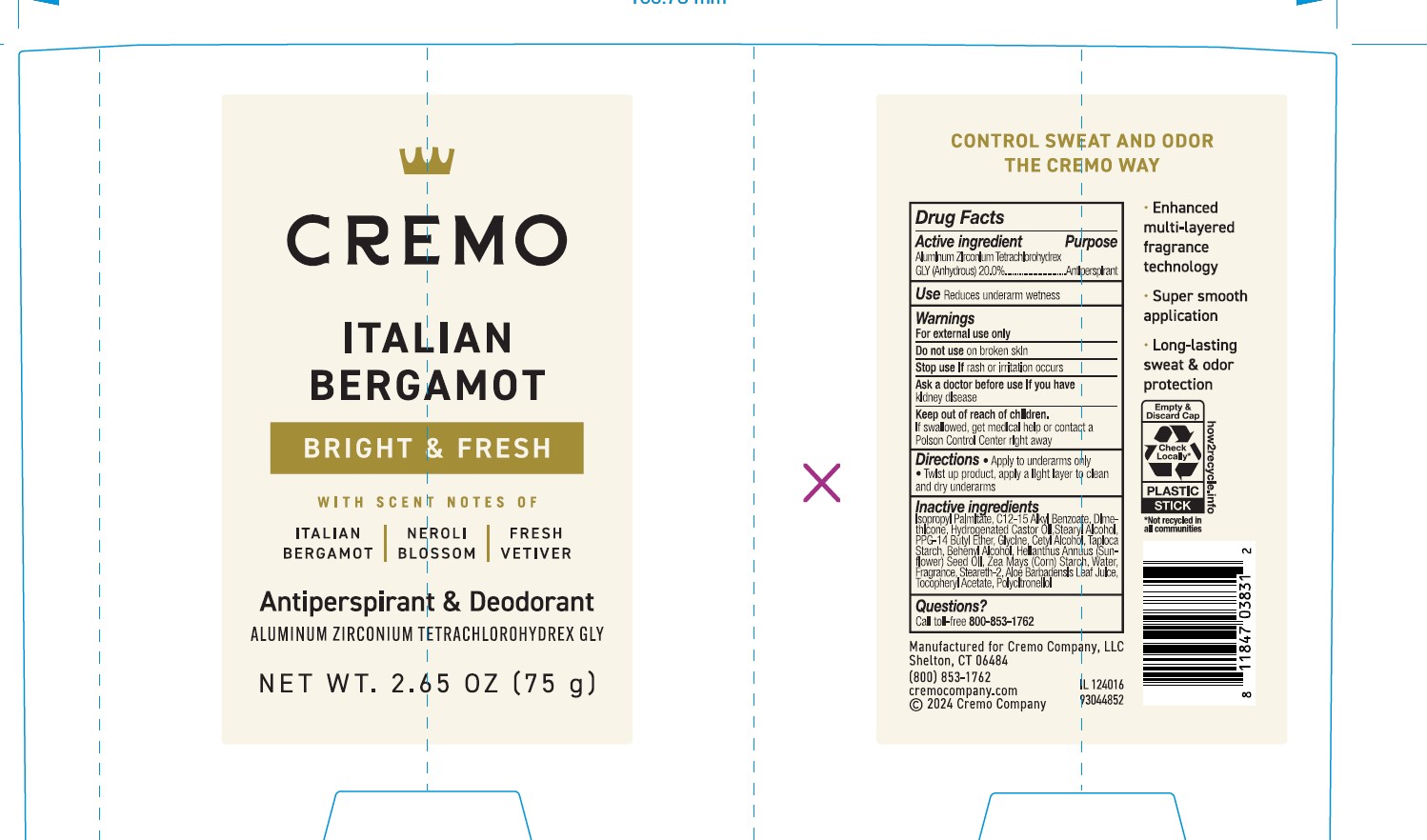 DRUG LABEL: Cremo Company
NDC: 71825-151 | Form: STICK
Manufacturer: Cremo Company, LLC
Category: otc | Type: HUMAN OTC DRUG LABEL
Date: 20241217

ACTIVE INGREDIENTS: ALUMINUM ZIRCONIUM TETRACHLOROHYDREX GLY 20 g/100 mL
INACTIVE INGREDIENTS: STEARYL ALCOHOL; CETYL ALCOHOL; C12-15 ALKYL BENZOATE; HYDROGENATED CASTOR OIL; STEARETH-2; BEHENYL ALCOHOL; HELIANTHUS ANNUUS (SUNFLOWER) SEED OIL; ISOPROPYL PALMITATE; ZEA MAYS (CORN) STARCH; ALOE BARBADENSIS LEAF JUICE; ALPHA-TOCOPHEROL ACETATE; TAPIOCA STARCH; WATER; DIMETHICONE, UNSPECIFIED; PPG-14 BUTYL ETHER; GLYCINE

Active Ingredient

Aluminum Zirconium Tetrachlorohydrex GLY (Anhydrous) 20%

Purpose

Antiperspirant

Uses

Reduces underarm wetness

Warnings

For external use only

Do not use

on broken skin.

Stop use if

rash or irritation occurs.

Ask a doctor before use if you have

kidney disease.

Keep out of reach of children.

If swallowed, get medical help or contact a Poison Control Center right away.

Directions

- Apply to underarms only
- Twist up product, apply a light layer to clean and dry underarms

Inactive Ingredients

Isopropyl Palmitate, C12-15 Alkyl Benzoate, Dimethicone, Hydrogenated Castor Oil, Stearyl Alcohol, PPG-14 Butyl Ether, Glycine, Cetyl Alcohol, Tapioca Starch, Behenyl Alcohol, Helianthus Annuus (Sunflower) Seed Oil, Zea Mays (Corn) Starch, Water, Fragrance, Steareth-2, Aloe Barbadensis Leaf Juice, Tocopheryl Acetate, Polycitronellol.

Questions?

Call toll-free 800-853-1762

Primary Display Panel

CREMO

ITALIAN BERGAMOT

BRIGHT & FRESH

WITH SCENT NOTES OF

ITALIAN BERGAMOT | NEROLI BLOSSOM | FRESH VETIVER

Antiperspirant & Deordorant

ALUMINUM ZIRCONIUM TETRACHLOROHYDREX GLY

NET WT. 2.65 OZ (75 g)